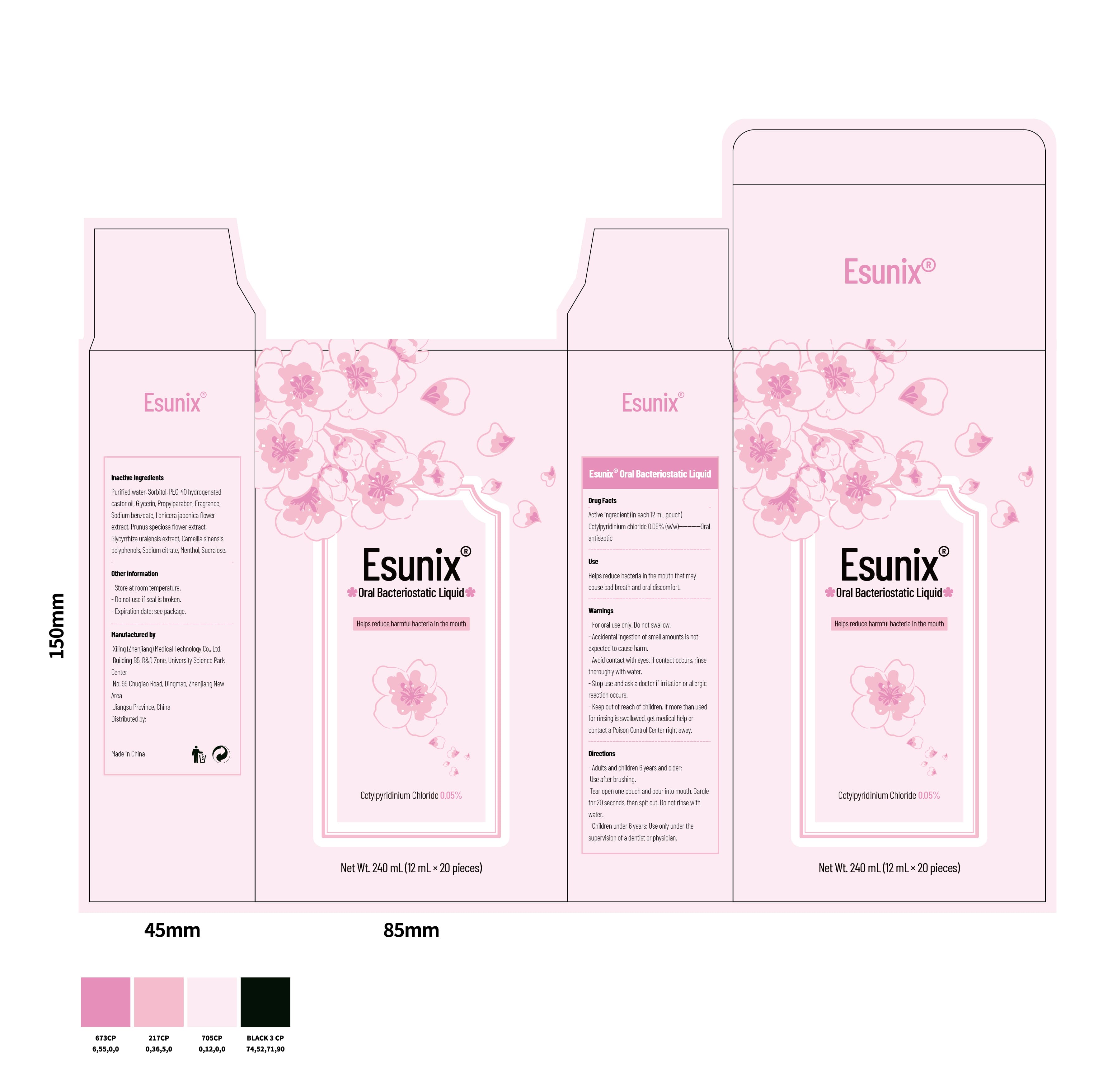 DRUG LABEL: Esunix Oral Bacteriostatic Liquid
NDC: 87118-005 | Form: LIQUID
Manufacturer: Xiling (Zhenjiang) Medical Technology Co., Ltd.
Category: otc | Type: HUMAN OTC DRUG LABEL
Date: 20250927

ACTIVE INGREDIENTS: CETYLPYRIDINIUM CHLORIDE 0.05 mg/100 mg
INACTIVE INGREDIENTS: SODIUM BENZOATE; SORBITOL; CAMELLIA SINENSIS LEAF; MENTHOL; GLYCYRRHIZA URALENSIS; SODIUM CITRATE; GLYCERIN; FRAGRANCE MINT ORC2000774; LONICERA JAPONICA FLOWER; PEG-40 HYDROGENATED CASTOR OIL; SUCRALOSE; PRUNUS SPECIOSA FLOWER; WATER; PROPYLPARABEN

ACTIVE INGREDIENT

Cetylpyridinium chloride 0.05% (w/w)

PURPOSE

Oral antiseptic

DOSAGE AND ADMINISTRATION

Adults and children 6 years and older:
Use after brushing. Tear open one pouch and pour into mouth. Gargle for 20 seconds, then spit out. Do not rinse with water.

Children under 6 years:
Use only under the supervision of a dentist or physician.

WARNINGS

For oral use only. Do not swallow.

Accidental ingestion of small amounts is not expected to cause harm.

Avoid contact with eyes. If contact occurs, rinse thoroughly with water.

Stop use and ask a doctor if irritation or allergic reaction occurs.

Keep out of reach of children. If more than used for rinsing is swallowed, get medical help or contact a Poison Control Center right away.

INDICATIONS AND USAGE

Helps reduce bacteria in the mouth that may cause bad breath and oral discomfort.

INACTIVE INGREDIENT

Purified water, Sorbitol, PEG-40 hydrogenated castor oil, Glycerin, Propylparaben, Fragrance, Sodium benzoate, Lonicera japonica flower extract, Prunus speciosa flower extract, Glycyrrhiza uralensis extract, Camellia sinensis polyphenols, Sodium citrate, Menthol, Sucralose.

keep out of reach of children section